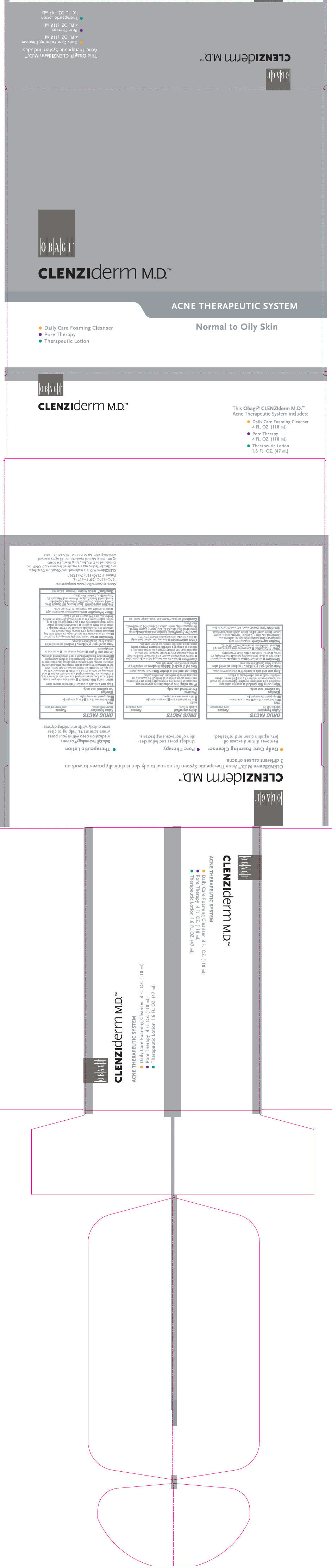 DRUG LABEL: CLENZIDERM NORMAL TO OILY SKIN 
NDC: 62032-511 | Form: KIT | Route: TOPICAL
Manufacturer: OMP, INC.
Category: otc | Type: HUMAN OTC DRUG LABEL
Date: 20120510

ACTIVE INGREDIENTS: SALICYLIC ACID 20 mg/1 mL; SALICYLIC ACID 20 mg/1 mL; BENZOYL PEROXIDE 50 mg/1 mL
INACTIVE INGREDIENTS: SODIUM LAURETH SULFATE; DIETHYLENE GLYCOL MONOETHYL ETHER; SODIUM LAURYL SULFATE; COCAMIDOPROPYL BETAINE; CETYL HYDROXYETHYLCELLULOSE (350000 MW); EDETATE DISODIUM; MENTHOL; MENTHYL LACTATE, (-)-; EXT. D&C VIOLET NO. 2; WATER; ALCOHOL; DIETHYLENE GLYCOL MONOETHYL ETHER; BENZYL ALCOHOL; 3-((L-MENTHYL)OXY)PROPANE-1,2-DIOL; GLYCERIN; BENZALKONIUM CHLORIDE; MENTHOL; MENTHYL LACTATE, (-)-; EXT. D&C VIOLET NO. 2; WATER; BENZYL BENZOATE; DICAPRYLYL ETHER; PROPYLENE GLYCOL; SQUALANE; POLYSORBATE 60; DIMETHYL ISOSORBIDE; PHENOXYETHANOL; EDETATE DISODIUM; BUTYLATED HYDROXYTOLUENE; WATER

CLENZIDERM NORMAL TO OILY SKIN
ACNE THERAPEUTIC SYSTEM

Daily Care Foaming Cleanser

DRUG FACTS

Active Ingredient

Salicylic Acid 2%

Purpose

Acne treatment gel

Uses

- for the treatment of acne
- dries up acne pimples
- helps prevent new acne pimples.

Warnings

For external use only.

When using this product

- using other topical acne medications at the same time or immediately following use of this product may increase dryness or irritation of the skin. If this occurs, only one medication should be used unless directed by a doctor.

Stop use and ask a doctor if

- irritation becomes severe.

Keep out of reach of children. If swallowed, get medical help or contact a Poison Control Center right away.

Directions

- use AM and PM
- wet face
- gently massage product all over face for 20–30 seconds avoiding eye area
- rinse thoroughly and pat dry
- wait 10–15 minutes to allow skin to dry completely.

Other Information

- store away from heat and direct sunlight
- store at controlled room temperature: 15°–25°C (59°–77°F).

Inactive Ingredients

Butyl Avocadate, Cetyl Hydroxyethylcellulose, Cocamidopropyl Betaine, Disodium EDTA, Ethoxydiglycol, Ext. Violet 2 (CI 60730), Fragrance, Menthol, Menthyl Lactate, Sodium Laureth Sulfate, Sodium Lauryl Sulfate, Water (Aqua).

Questions?

(800) 636-7546 Mon–Fri 9:00 am–4:00 pm Pacific Time

Pore Therapy

DRUG FACTS

Active Ingredient

Salicylic Acid 2%

Purpose

Acne treatment

Uses

- for the treatment of acne
- dries up acne pimples
- helps prevent new acne pimples.

Warnings

For external use only.

When using this product

- using other topical acne medications at the same time or immediately following use of this product may increase dryness or irritation of the skin. If this occurs, only one medication should be used unless directed by a doctor.

Stop use and ask a doctor if

- irritation becomes severe.

Keep out of reach of children. If swallowed, get medical help or contact a Poison Control Center right away.

Directions

- cleanse the skin thoroughly before applying medication
- cover the entire affected area with a thin layer one to three times daily
- because excessive drying of the skin may occur, start with one application daily, then gradually increase to two or three times daily if needed or as directed by a doctor
- if bothersome dryness or peeling occurs, reduce application to once a day or every other day.

Other Information

- store away from heat and direct sunlight
- store at controlled room temperature: 15°–25°C (59°–77°F).

Inactive Ingredients

Benzalkonium Chloride, Benzyl Alcohol, Ethoxydiglycol, Ext. Violet 2 (CI 60730), Fragrance, Glycerin, Menthol, Menthoxypropanediol, Menthyl Lactate, SD Alcohol 40-B (Alcohol Denat.), Water (Aqua).

Questions?

(800) 636-7546 Mon–Fri 9:00 am–4:00 pm Pacific Time

Therapeutic Lotion

DRUG FACTS

Active Ingredient

Benzoyl Peroxide 5%

Purpose

Acne treatment lotion

Uses

- for the treatment of acne
- dries up acne pimples
- helps prevent new acne pimples.

Warnings

For external use only.

Stop use and ask a doctor if

- irritation becomes severe.

When using this product

- skin irritation and dryness is more likely to occur if you use another topical acne medication at the same time. If irritation occurs, only use one topical acne medication at a time
- avoid unnecessary sun exposure and use a sunscreen
- avoid contact with the eyes, lips, and mouth
- avoid contact with hair and dyed fabrics, which may be bleached by this product
- skin irritation may occur, characterized by redness, burning, itching, peeling, or possibly swelling. Irritation may be reduced by using the product less frequently or in a lower concentration
- if pregnant or breast-feeding, ask a health care professional before use.

Do not use if you

- have very sensitive skin
- are sensitive to benzoyl peroxide.

Keep out of reach of children. If swallowed, get medical help or contact a Poison Control Center right away.

Directions

- clean the skin thoroughly before applying this product
- cover the entire affected area with a thin layer one to three times daily
- because excessive drying of the skin may occur, start with one application daily, then gradually increase to two or three times daily if needed or as directed by a doctor
- if bothersome dryness or peeling occurs, reduce application to once a day or every other day
- if going outside, apply sunscreen after using this product. If irritation or sensitivity develops, stop use of both products and ask a doctor.

Other Information

- store away from heat and direct sunlight
- store at controlled room temperature: 15°–25°C (59°–77°F).

Inactive Ingredients

Benzyl Benzoate, BHT, Dicaprylyl Ether, Dimethyl Isosorbide, Disodium EDTA, Hydroxyethyl Acrylate/Sodium Acryloyldimethyl Taurate Copolymer, Phenoxyethanol, Polysorbate 60, Propylene Glycol, Squalane, Water (Aqua).

Questions?

1-800-636-7546 Mon–Fri 9:00 am–4:00 pm PST

Distributed by OMP, Inc., Long Beach, CA 90806

PRINCIPAL DISPLAY PANEL - Kit Carton

OBAGI®

CLENZIderm M.D.™

ACNE THERAPEUTIC SYSTEM

- Daily Care Foaming Cleanser
- Pore Therapy
- Therapeutic Lotion

Normal to Oily Skin